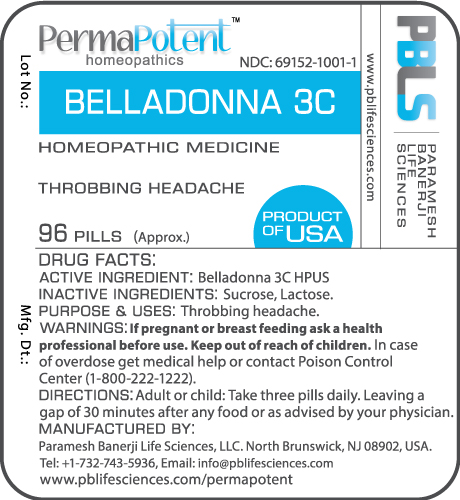 DRUG LABEL: Belladonna 3C
NDC: 69152-1001 | Form: PELLET
Manufacturer: Paramesh Banerji Life Sciences LLC
Category: homeopathic | Type: HUMAN OTC DRUG LABEL
Date: 20160713

ACTIVE INGREDIENTS: ATROPA BELLADONNA 3 [hp_C]/1 1
INACTIVE INGREDIENTS: SUCROSE; LACTOSE

DRUG FACTS: Active Ingredient

Belladonna 3C HPUS

Inactive Ingredients

Sucrose, Lactose

Purpose

Throbbing headache

Uses

Throbbing headache

Warnings

If pregnant or breast feeding ask a health professional before use.

Keep out of reach of children. In case of overdose, get medical help or contact a Poison Control Center (1-800-222-1222) right away.

Direction

Adult or child: Take three pills daily. Leaving a gap of 30 minutes after any food or as advised by your physician.

Manufactured by

Paramesh Banerji Life Sciences, LLC.

North Brunswick, NJ 08902, USA.

Tel: +1-732-743-5936,

Email: info@pblifesciences.com

www.pblifesciences.com/permapotent

Principal Display Panel

NDC: 69152-1001-1

Belladonna 3C

Homeopathic Medicine

Throbbing headache

96 Pills (Approx.)

Product of USA